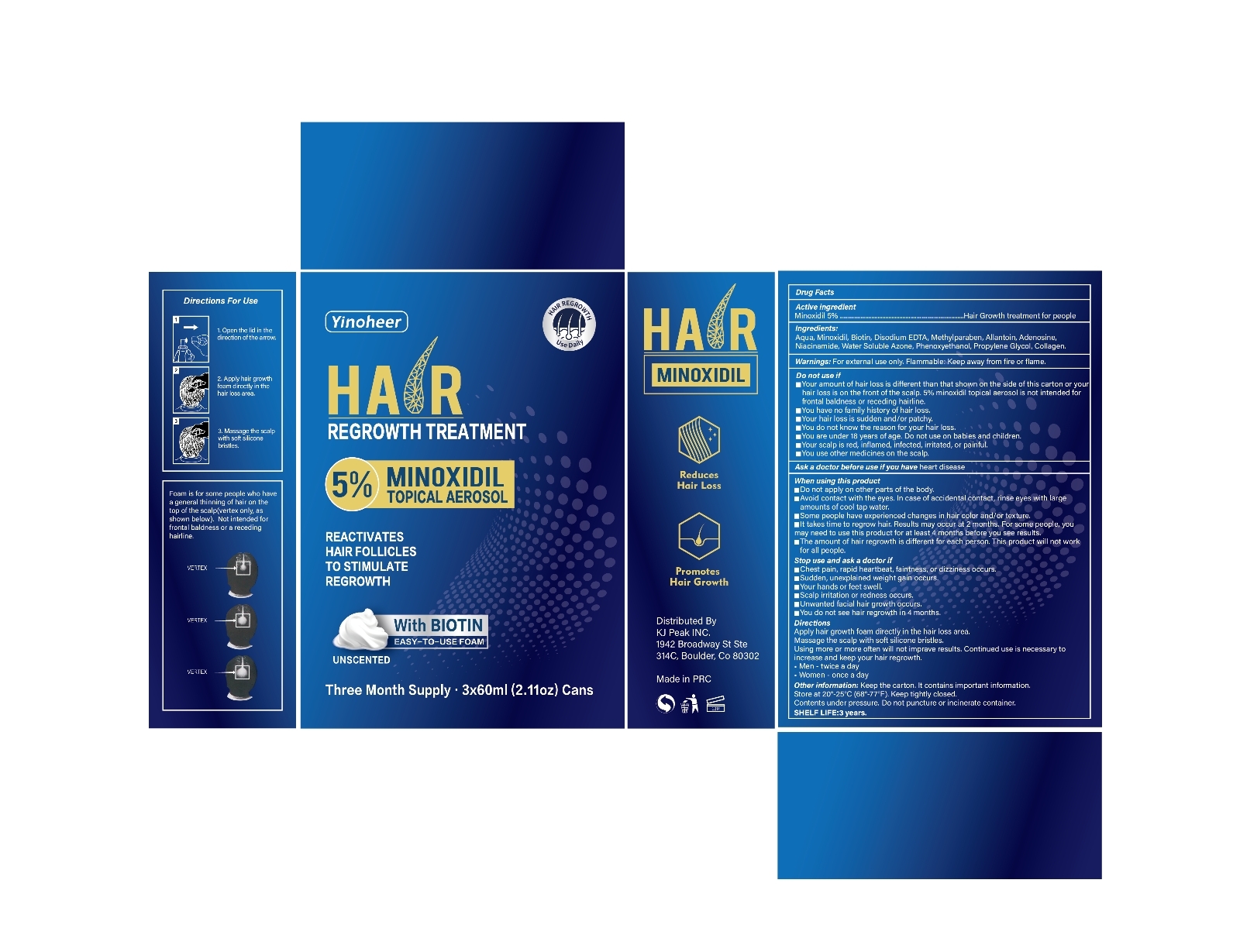 DRUG LABEL: Hair Regrowth 5% Minoxidil
NDC: 84033-008 | Form: AEROSOL, FOAM
Manufacturer: Qingdao Kuajie Online Electronic Technology Co., Ltd
Category: otc | Type: HUMAN OTC DRUG LABEL
Date: 20241216

ACTIVE INGREDIENTS: MINOXIDIL 5 g/100 mL
INACTIVE INGREDIENTS: WATER 66.3 mL/100 mL; BIOTIN 4.3 g/100 mL; POTASSIUM METHYLPARABEN 0.2 g/100 mL; PHENOXYETHANOL 0.8 g/100 mL; ADENOSINE 1.5 g/100 mL; NIACINAMIDE 3.5 g/100 mL; LAUROCAPRAM 2 g/100 mL; LAURAMIDOPROPYL PROPYLENE GLYCOL-DIMONIUM CHLORIDE PHOSPHATE 15 g/100 mL; CALCIUM DISODIUM EDTA 0.2 g/100 mL; ALLANTOIN BIOTIN 0.5 g/100 mL; MARINE COLLAGEN, SOLUBLE 0.7 g/100 mL

ACTIVE INGREDIENT

MINOXIDIL 5%

INACTIVE INGREDIENT

Aqua 66.3
Biotin 4.3
Disodium EDTA 0.2
Methylparaben 0.2
Allantoin 0.5
Adenosine 1.5
Niacinamide 3.5
Water Soluble Azone 2
Phenoxyethanol 0.8
Propylene Glycol 15
Collagen 0.7

PURPOSE

Hair Growth

HOW TO USE

Apply 1 ML(few drops)directly onto scalp on the hair loss area.
Use fingertips to massage solution into skin/hair for 2-3 minutes or use a roller to roll 4-5 times.
Allow time for hair to fully absorb Growth Oil, don't apply anything to your hair for a few hours.

WARNINGS

Flammable : Keep away from fire or flame.
Keep out of reach of children.

STOP USE AND ASK A DOCTOR IF

Chest pain, rapid heartbeat, faintness, or dizziness occurs
Sudden, unexplained weight gain occurs
Your hands or feet swell
Scalp irritation or redness occurs
Unwanted facial hair growth occurs
You do not see hair regrowth in 4 months

DO NOT USE IF

your hair loss is on the front of the scalp. 5% minoxidil topical solution is not intended for frontal baldness or receding hairline.
you have no family history of hair loss.
your hair loss is sudden and/or patchy.
you do not know the reason for your hair loss.
you are under 18 years of age. Do not use on babies and children.
your scalp is red, inflamed, infected, irritated, or painful.
you use other medicines on the scalp.
Ask a doctor before use if you have heart disease.
May be harmful if used when pregnant or breast-feeding.

WHEN USING THIS PRODUCT

Do not apply on other parts of the body.
Avoid contact with the eyes. In case of accidental contact, rinse eyes with large amounts of cool tap water.
Some people have experienced changes in hair color and/or texture.
It takes time to regrow hair. Results may occur at 2 months with twice a day usage.
For some men, you may need to use this product for at least 4 months before you see results.
The amount of hair regrowth is different for each person.
This product will not work for all men.

STORAGE

Store in a dark, cool place.
Store at controlled room temperature 59°F-77°F(15°C-25°C).
Keep out of direct sunlight.
Keep the cap on tightly when not in use.

KEEP OUT OF REACH OF CHILDREN

Flammable : Keep away from fire or flame.
Keep out of reach of children.

DOSAGE

Apply 1 ML(few drops)directly onto scalp on the hair loss area.
Use fingertips to massage solution into skin/hair for 2-3 minutes or use a roller to roll 4-5 times.
Allow time for hair to fully absorb Growth Oil, don't apply anything to your hair for a few hours.